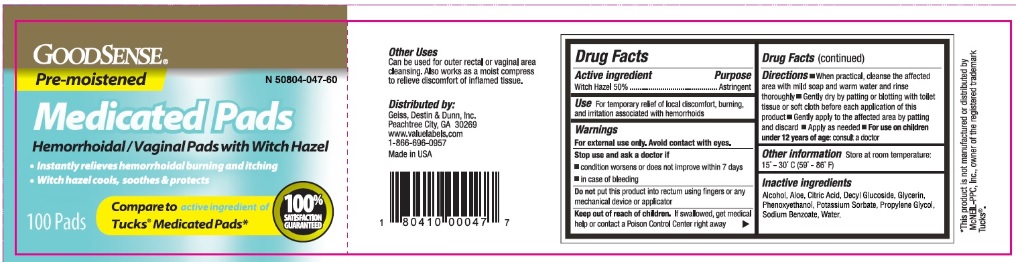 DRUG LABEL: Good Sense
NDC: 50804-047 | Form: CLOTH
Manufacturer: Geiss, Destin & Dunn, Inc
Category: otc | Type: HUMAN OTC DRUG LABEL
Date: 20251205

ACTIVE INGREDIENTS: WITCH HAZEL 500 mg/1 1
INACTIVE INGREDIENTS: ALCOHOL; WATER; GLYCERIN; PHENOXYETHANOL; ALOE; DECYL GLUCOSIDE; POTASSIUM SORBATE; PROPYLENE GLYCOL; SODIUM BENZOATE; CITRIC ACID MONOHYDRATE

Drug Facts

Active ingredient

Witch hazel 50%

Purpose

Astringent

Uses

For temporary relief of local discomfort, burning and irritation associated with hemorrhoids

Warnings

For external use only. Avoid contact with eyes.

Stop use and ask a doctor if

- condition worsens or does not improve within 7 days
- in case of bleeding

Do Not Use

Do not put this product into rectum using fingers or any mechanical device or applicator

Keep out of reach of children.

If swallowed, get medical help or contact a Poison Control Center right away.

Directions

- When practical, cleanse the affected area with mild soap and warm water and rinse thoroughly
- Gently dry by patting or blotting with toilet tissue or soft cloth before each application of this product
- Gently apply to the affected area by patting and discard
- Apply as needed
- For use on children under 12 years of age: consult a doctor

Other information

Store at room temperature: 15o C - 30o C (59 - 86o F)

Inactive ingredients

Alcohol, Aloe, Citric Acid, Decyl Glucoside, Glycerin, Phenoxyethanol, Potassium Sorbate, Propylene Glycol, Sodium Benzoate, Water.

Principal Display Panel

GOOD SENSE

Pre-moistened

N 50804-047-60

Medicated Pads

Hemorrhoidal/Vaginal Pads with Witch Hazel

- Instantly relieves hemorrhoidal burning and itching
- Witch hazel cools, soothes and protects

Compare to the active ingredient in Tucks®* Medicated Pads*

100% SATISFACTION GURANTEED

*This product is not manufactured or distributed by McNEIL-PPC, Inc., owner of the registered trademark Tucks®.